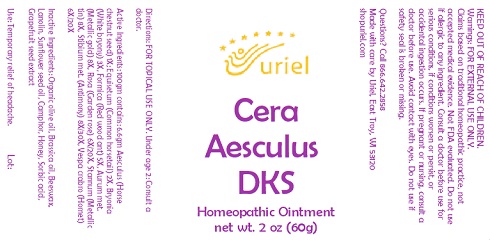 DRUG LABEL: Cera Aesculus DKS
NDC: 48951-3254 | Form: OINTMENT
Manufacturer: Uriel Pharmacy Inc.
Category: homeopathic | Type: HUMAN OTC DRUG LABEL
Date: 20231002

ACTIVE INGREDIENTS: HORSE CHESTNUT 1 [hp_X]/1 g; EQUISETUM ARVENSE TOP 2 [hp_X]/1 g; BRYONIA ALBA ROOT 3 [hp_X]/1 g; FORMICA RUFA 5 [hp_X]/1 g; GOLD 8 [hp_X]/1 g; SEDUM ROSEUM WHOLE 6 [hp_X]/1 g; TIN 8 [hp_X]/1 g; ANTIMONY 8 [hp_X]/1 g; VESPA CRABRO 6 [hp_X]/1 g
INACTIVE INGREDIENTS: SORBIC ACID; OLIVE OIL; BRASSICA JUNCEA SEED OIL; YELLOW WAX; LANOLIN; SUNFLOWER OIL; CAMPHOR (NATURAL); HONEY; CITRUS PARADISI SEED

Cera Aesculus DKS

INDICATIONS AND USAGE

Directions: FOR TOPICAL USE ONLY.

DOSAGE AND ADMINISTRATION

Under age 2: Consult a doctor.

ACTIVE INGREDIENT

Active Ingredients: 100gm contains: 6.6gm Aesculus (Horse chestnut seed) 1X; Equisetum (Common horsetail) 2X, Bryonia (White bryony) 3X, Formica (Red wood ant) 5X, Aurum (Metallic gold) 8X, Rosa (Garden rose) 6X/20X, Stannum (Metallic tin) 8X, Stibium met. (Antimony) 8X/30X, Vespa crabro (Hornet) 6X/20X

INACTIVE INGREDIENT

Inactive Ingredients: Organic olive oil, Brassica oil, Beeswax, Lanolin, Sunflower seed oil, Camphor, Honey, Sorbic Acid, Grapefruit seed extract

PURPOSE

Use: Temporary relief of headache.

KEEP OUT OF REACH OF CHILDREN.

Warnings: FOR EXTERNAL USE ONLY.
Claims based on traditional homeopathic practice, not accepted medical evidence. Not FDA evaluated. Do not use if allergic to any ingredient. Consult a doctor before use for serious conditions, if conditions worsen or persist, or accidental ingestion occurs. If pregnant or nursing, consult a doctor before use. Avoid contact with eyes. Do not use if safety seal is broken or missing.

QUESTIONS

Questions? Call 866.642.2858 Made with care by Uriel, East Troy, WI 53120 shopuriel.com